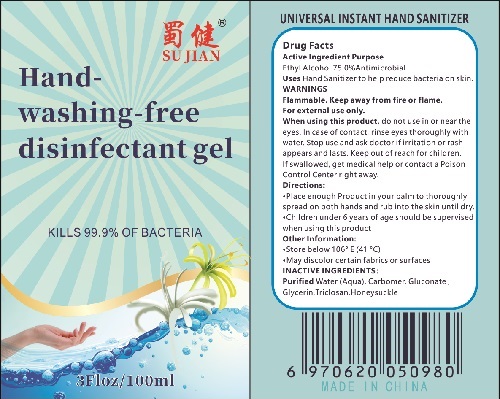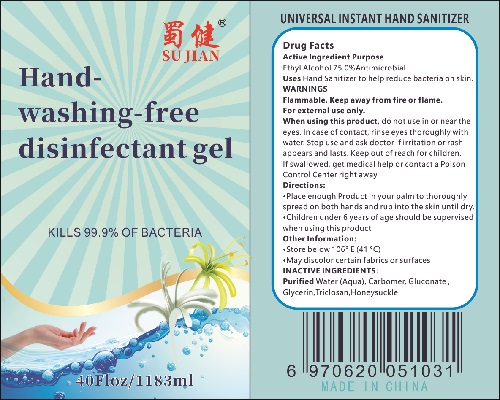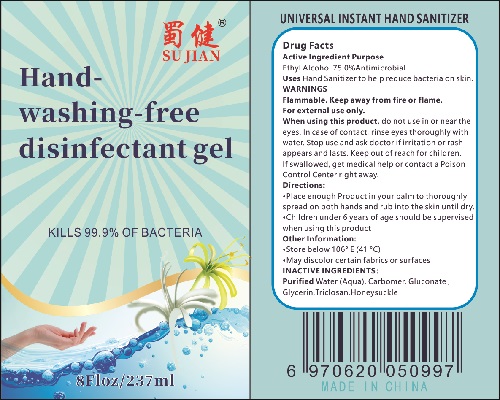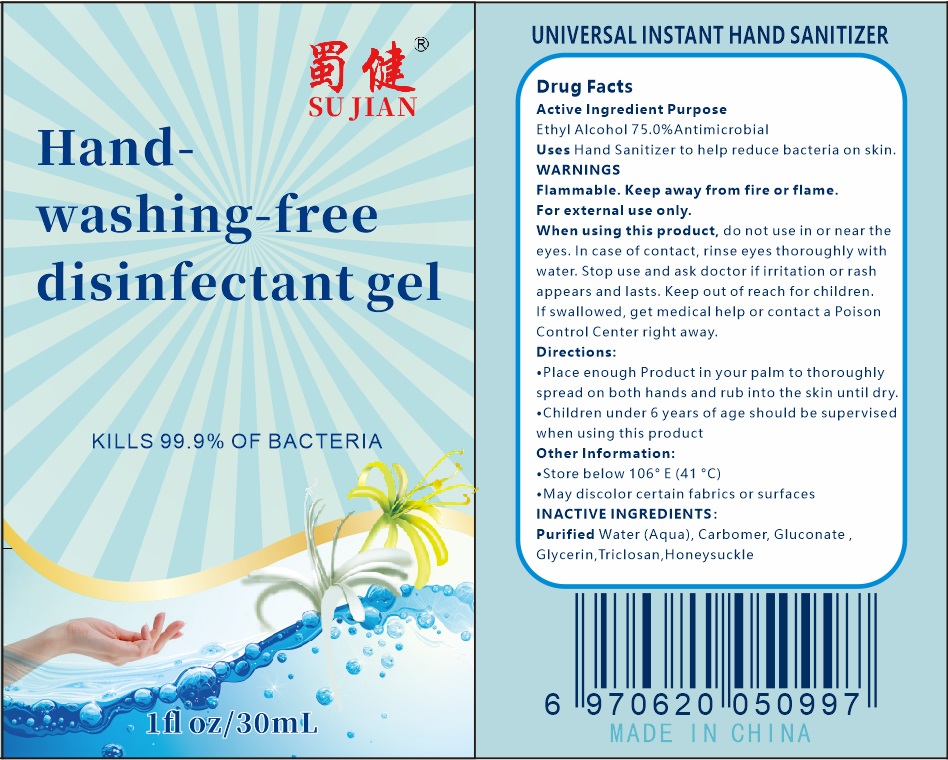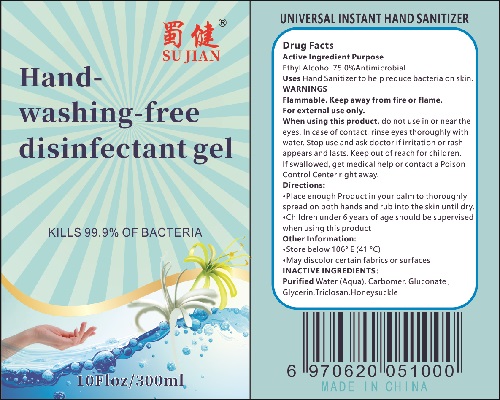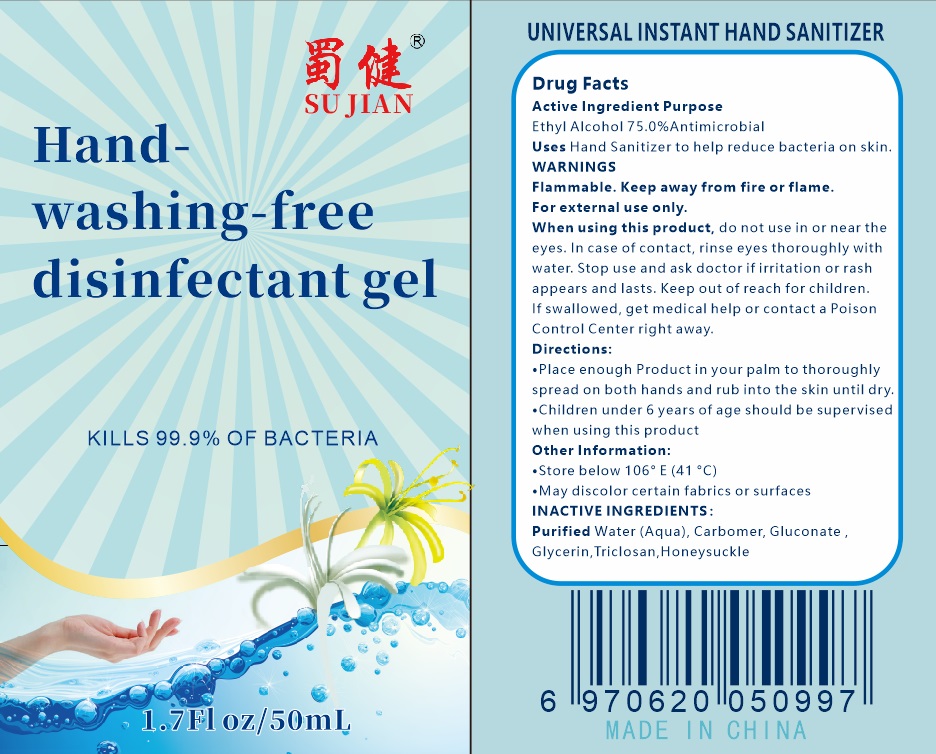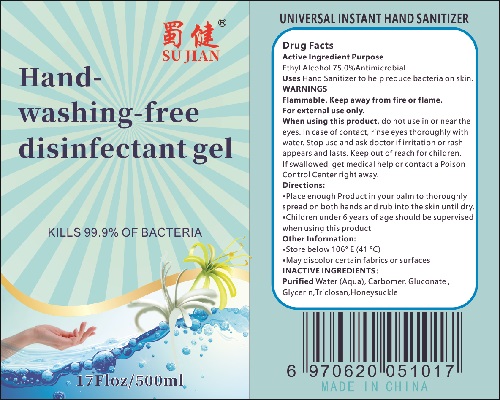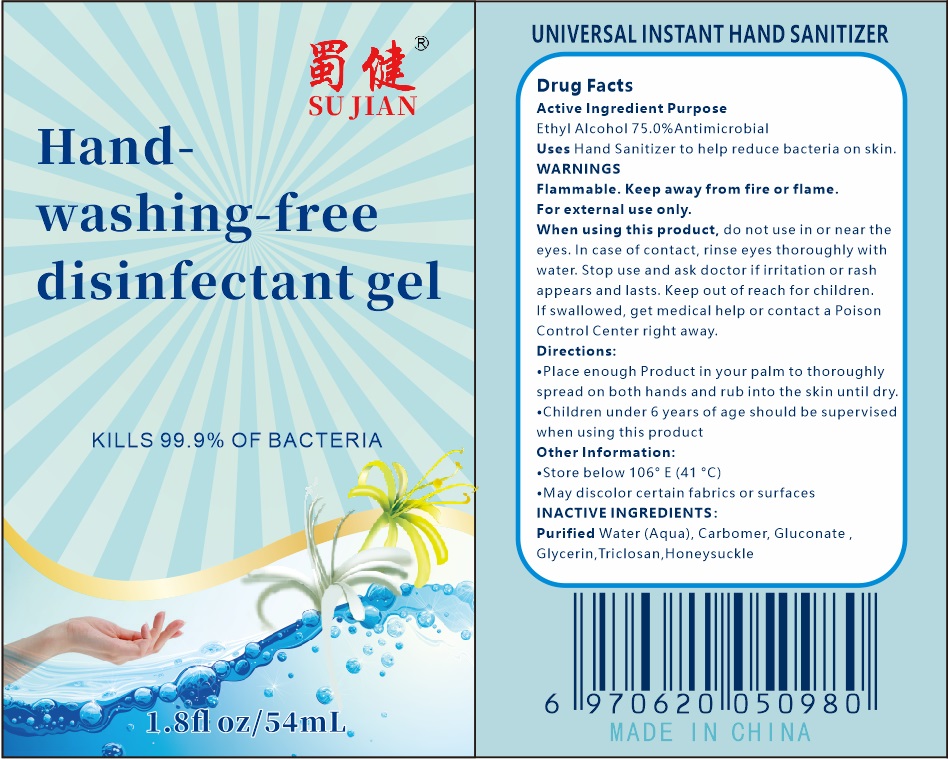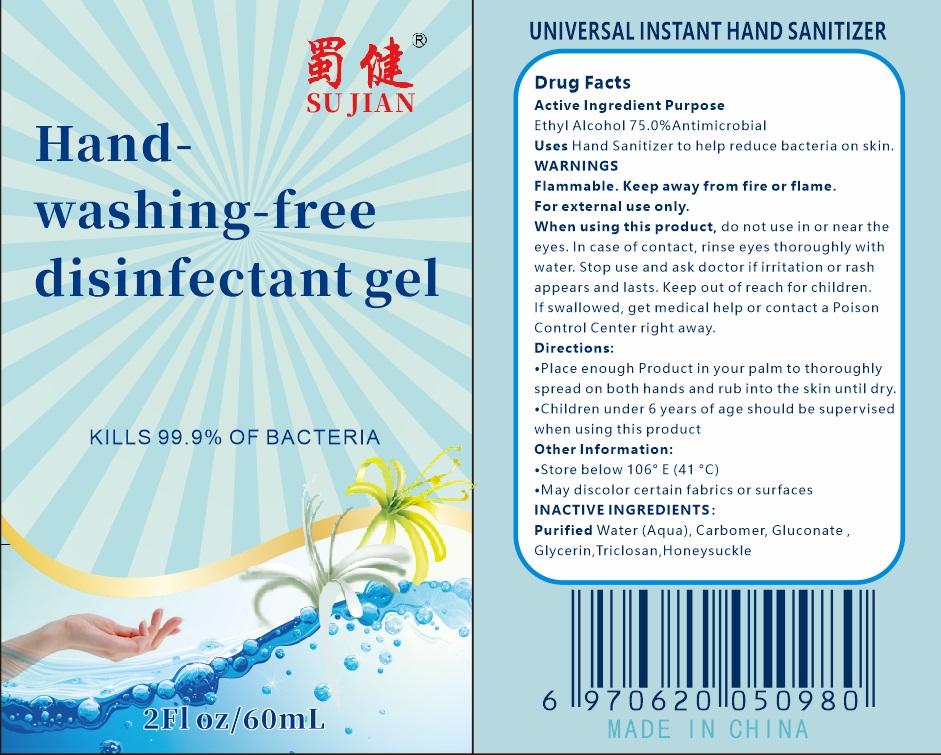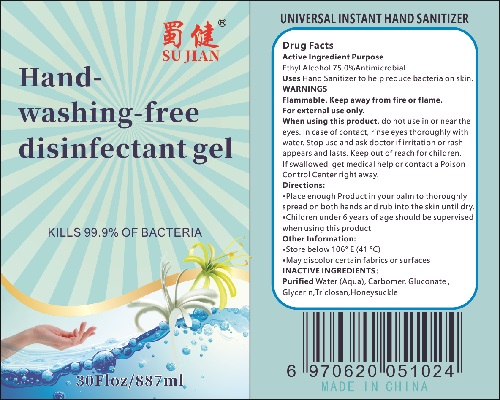 DRUG LABEL: Universal Instant Hand Sanitizer
NDC: 74034-005 | Form: LIQUID
Manufacturer: Sichuan Rejoy Essence Biotechnology Co., Ltd
Category: otc | Type: HUMAN OTC DRUG LABEL
Date: 20200417

ACTIVE INGREDIENTS: ALCOHOL 75 mL/100 mL
INACTIVE INGREDIENTS: GLUCONATE ION; LONICERA CAPRIFOLIUM FLOWER; TRICLOSAN; GLYCERIN; CARBOMER 934; WATER

Active Ingredient(s)

Alcohol 75% v/v. Purpose: Antiseptic

Purpose

Antiseptic, Hand Sanitizer

Uses

Hand Sanitizer to help reduce bacteria on skin.

WARNINGS

Flammable. Keep away from fire or flame.For external use only

When using this product,do not use in or near the eyes. In case of contact, rinse eyes thoroughly with water Stop use and ask doctor if irritation or rash appears and lasts.

When using this product keep out of eyes, ears, and mouth. In case of contact with eyes, rinse eyes thoroughly with water.
Stop use and ask a doctor if irritation or rash occurs. These may be signs of a serious condition.
Keep out of reach of children. If swallowed, get medical help or contact a Poison Control Center right away.

Stop use and ask a doctor if irritation or rash occurs. These may be signs of a serious condition.

When using this product

Keep out of reach of children. If swallowed, get medical help or contact a Poison Control Center right away.

Directions

- Place enough product on hands to cover all surfaces. Rub hands together until dry.
- Children under 6 years of age should be supervised when using this product

Other information

- Store below 106F(41C)
- May discolor certain fabrics or surfaces

Inactive ingredients

Purified Water(Aqua), Carbomer, Gluconate Glycerin, Triclosan, Honeysuckle.